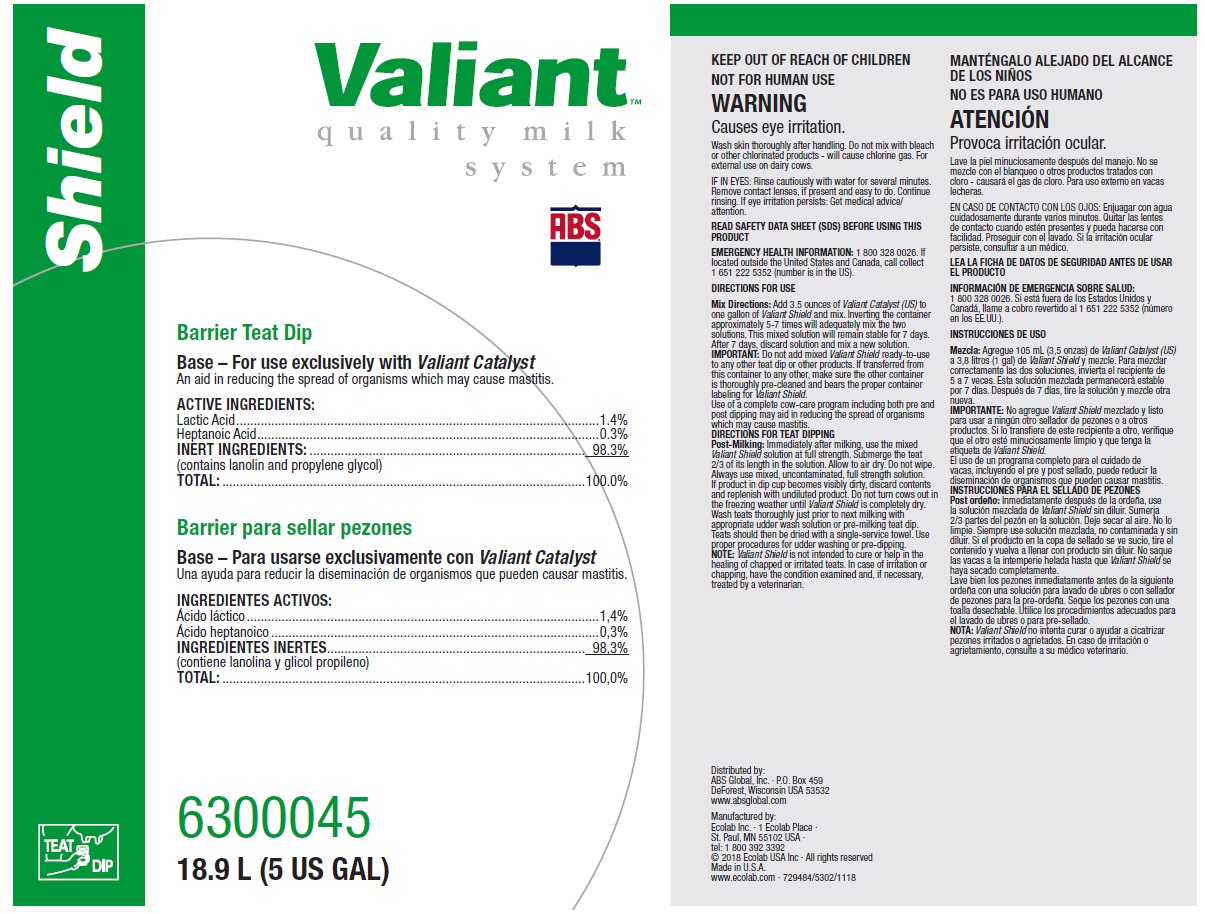 DRUG LABEL: Valiant Shield
NDC: 59282-112 | Form: SOLUTION
Manufacturer: ABS Global Inc.
Category: animal | Type: OTC ANIMAL DRUG LABEL
Date: 20190125

ACTIVE INGREDIENTS: LACTIC ACID 14 mg/1 mL; HEPTANOIC ACID 3 mg/1 mL
INACTIVE INGREDIENTS: WATER; PROPYLENE GLYCOL; LANOLIN

KEEP OUT OF REACH OF CHILDREN

NOT FOR HUMAN USE

WARNING

Causes eye irritation.

Wash skin thoroughly after handling. Do not mix with bleach or other chlorinated products - will cause chlorine gas. For external use on dairy cows.

VETERINARY INDICATIONS

DIRECTIONS FOR USE

Mix Directions: Add 3.5 ounces of Valiant Catalyst (US) to one gallon of Valiant Shield and mix. Inverting the container approximately 5-7 times will adequately mix the two solutions. This mixed solution will remain stable for 7 days. After 7 days, discard solution and mix a new solution.

IMPORTANT: Do not add mixed Valiant Shield ready-to-use to any other teat dip or other products. If transferred from this container to any other, make sure the other container is thoroughly pre-cleaned and bears the proper container labeling for Valiant Shield.

Use of a complete cow-care program including both pre and post dipping may aid in reducing the spread of organisms which may cause mastitis.

DIRECTIONS FOR TEAT DIPPING

Post-Milking: Immediately after milking, use the mixed Valiant Shield solution at full strength. Submerge the teat 2/3 of its length in the solution. Allow to air dry. Do not wipe. Always use mixed, uncontaminated, full strength solution. If product in dip cup becomes visibly dirty, discard contents and replenish with undiluted product. Do not turn cows out in the freezing weather until Valiant Shield is completely dry. Wash teats thoroughly just prior to next milking with appropriate udder wash solution or pre-milking teat dip. Teats should then be dried with a single-service towel. Use proper procedures for udder washing or pre-dipping.

NOTE: Valiant Shield is not intended to cure or help in the healing of chapped or irritated teats. In case of irritation or chapping, have the condition examined and, if necessary, treated by a veterinarian.

OTHER SAFETY INFORMATION

IF IN EYES: Rinse cautiously with water for several minutes. Remove contact lenses, if present and easy to do. Continue rinsing. If eye irritation persists: Get medical advice/ attention.

READ SAFETY DATA SHEET (SDS) BEFORE USING THIS PRODUCT

EMERGENCY HEALTH INFORMATION: 1 800 328 0026. If located outside the United States and Canada, call collect 1 651 222 5352 (number is in the US).

PACKAGE LABEL

Valiant

quality milk system

ABS

Shield

Barrier Teat Dip

Base - For use exclusively with Valiant Catalyst

An aid in reducing the spread of organisms which may cause mastitis

ACTIVE INGREDIENTS:

Lactic Acid...........................1.4%

Heptanoic Acid.......................0.3%

INERT INGREDIENTS:..............98.3%

(contains lanolin and propylene glycol)

TOTAL:...................................100.0%

6300045

18.9 L (5 US GAL)

Distributed by:

ABS Global, Inc. ∙ P.O. Box 459

DeForest, Wisconsin USA 53532

www.absglobal.com

Manufactured by:

Ecolab Inc. ∙ 1 Ecolab Place ∙

St. Paul, MN 55102 USA ∙

tel: 1 800 392 3392

© 2018 Ecolab USA Inc ∙ All rights reserved

Made in U.S.A.

www.ecolab.com ∙ 729484/5302/1118